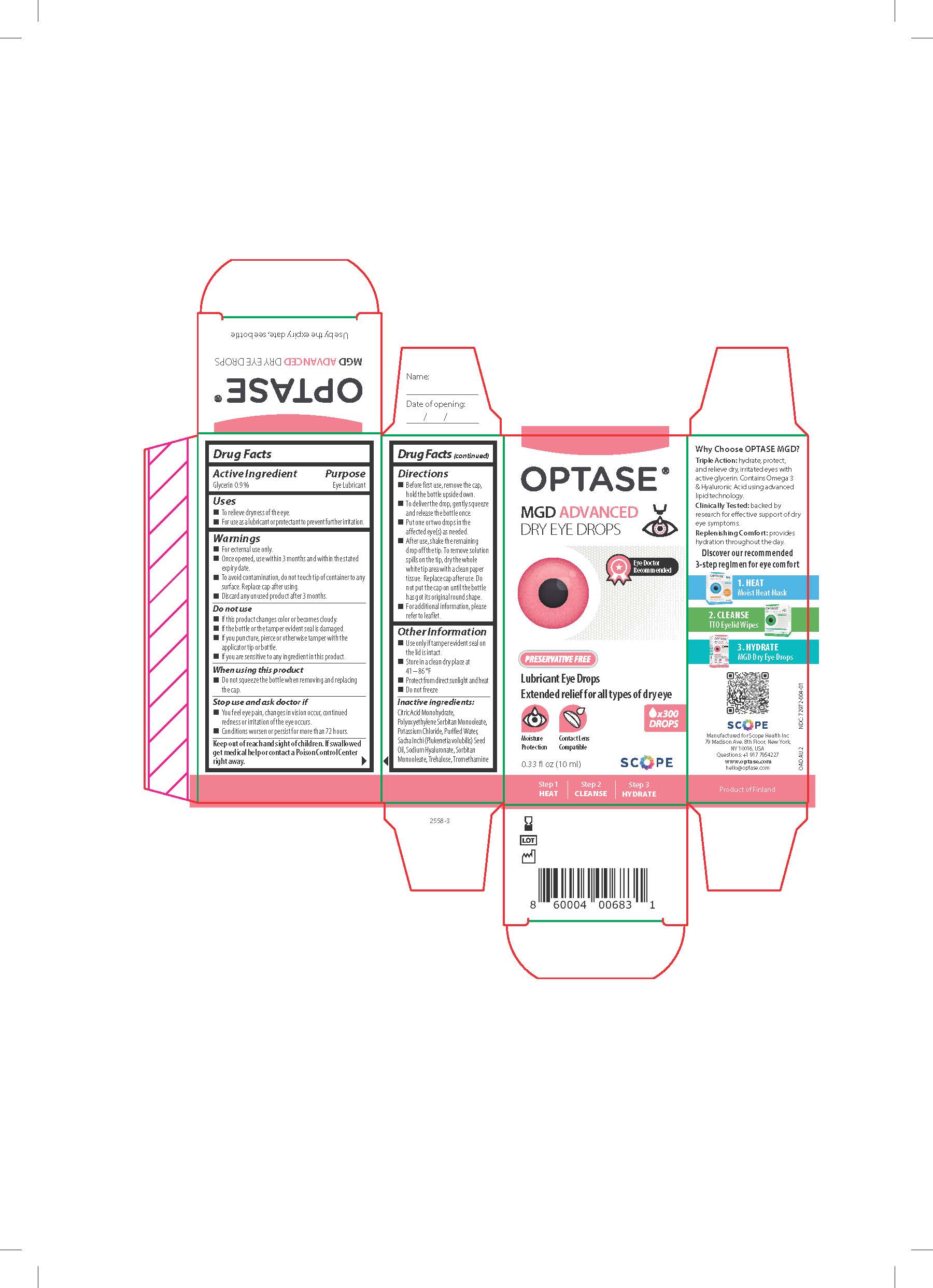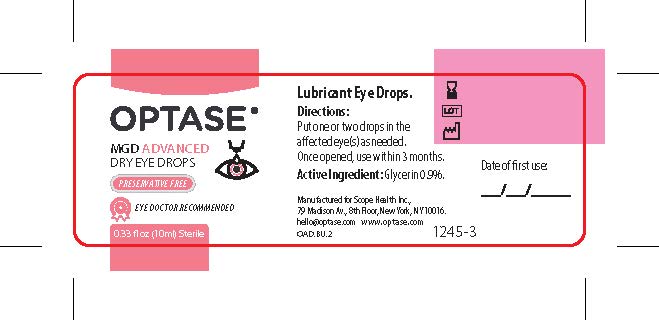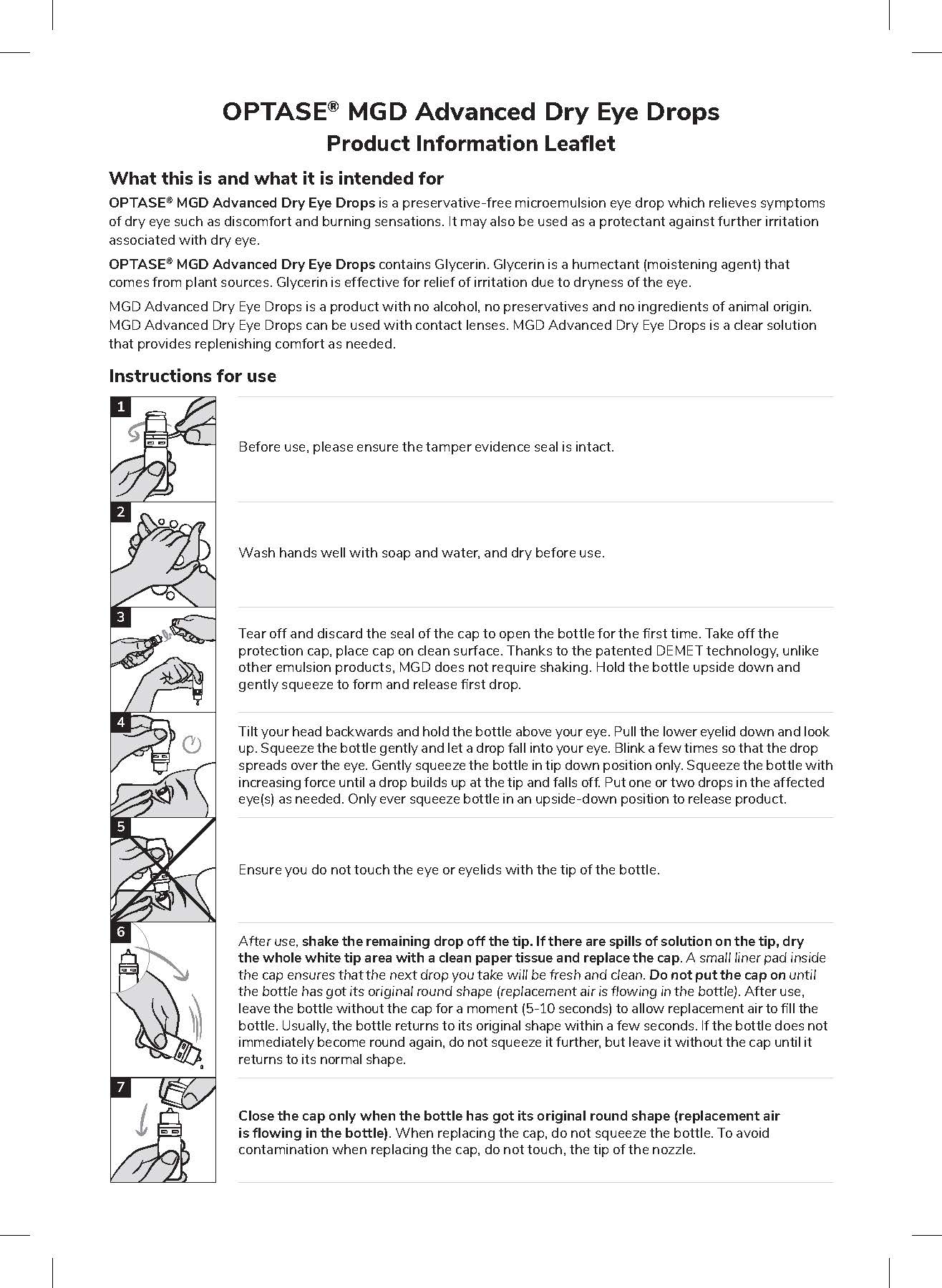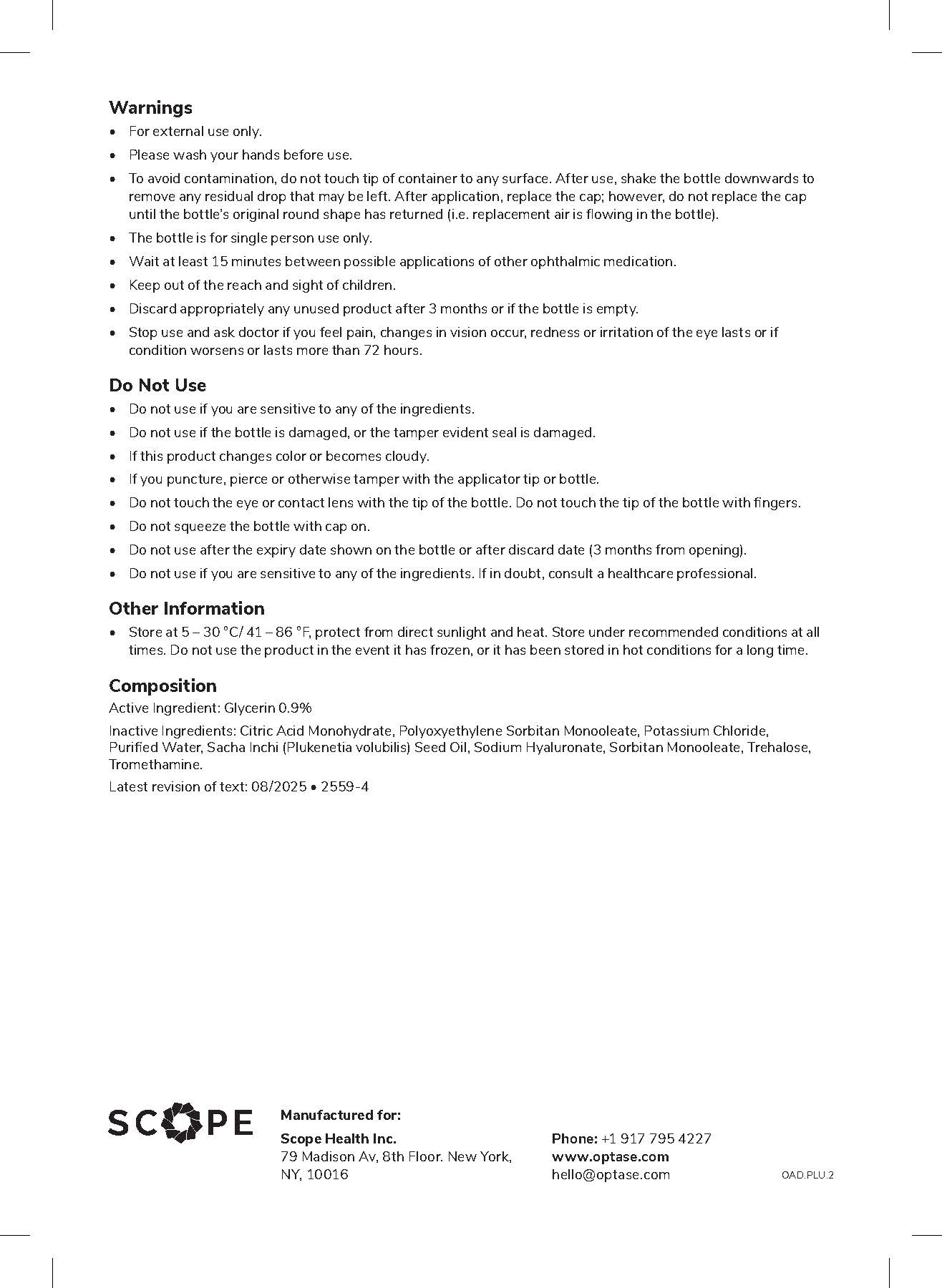 DRUG LABEL: Optase
NDC: 72972-004 | Form: SOLUTION/ DROPS
Manufacturer: Scope Health Inc
Category: otc | Type: HUMAN OTC DRUG LABEL
Date: 20260130

ACTIVE INGREDIENTS: GLYCERIN 9 mg/1 mL
INACTIVE INGREDIENTS: POLYSORBATE 80; TREHALOSE; HYALURONATE SODIUM; CITRIC ACID MONOHYDRATE; WATER; TROMETHAMINE; SORBITAN MONOOLEATE; POTASSIUM CHLORIDE; PLUKENETIA VOLUBILIS SEED OIL

Optase MGD Advanced Dry Eye Drops

ACTIVE INGREDIENT

Glycerin 0.9%

Keep Out of Reach of Children

If swallowed, get medical help or contact a poison control center right away.

PURPOSE

Eye Lubricant

Warning
• For external use only.
• To avoid contamination, do not touch tip
of container to any surface. After use, shake the bottle
downwards in order to remove any residual drop that
may be left. Replace cap after using.
• Do not use the solution if it changes color or becomes
cloudy
Stop use and ask doctor if
• You feel eye pain.
• Changes in vision occur.
• Redness or irritation of the eye lasts.
• Condition worsens or lasts more than 72 hours.

Uses

• For use as a lubricant to prevent further irritation.
• May be used as a protectant against further irritation.
• To relieve dryness of the eye.

Directions
Put one or two drops in the affected eyes as needed.

INACTIVE INGREDIENT

Citric Acid Monohydrate, Polyoxyethylenesorbitan Monooleate, Potassium Chloride, Purified Water, Saccha Inchi Seed Oil, Sodium Hyaluronate , Sorbitan Monooleate, Trehalose, Tromethamine